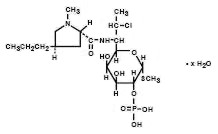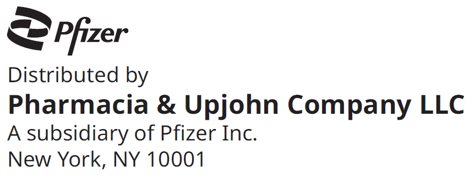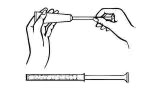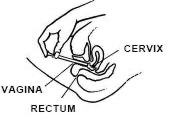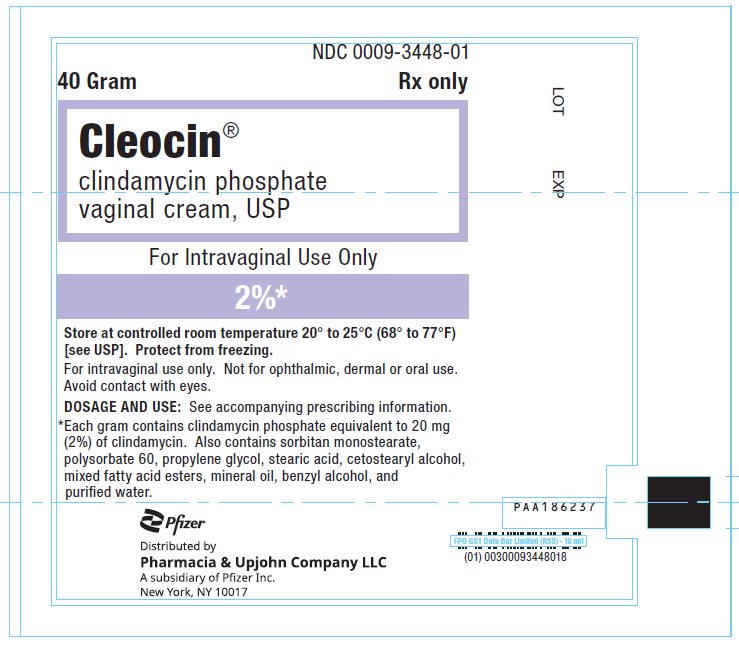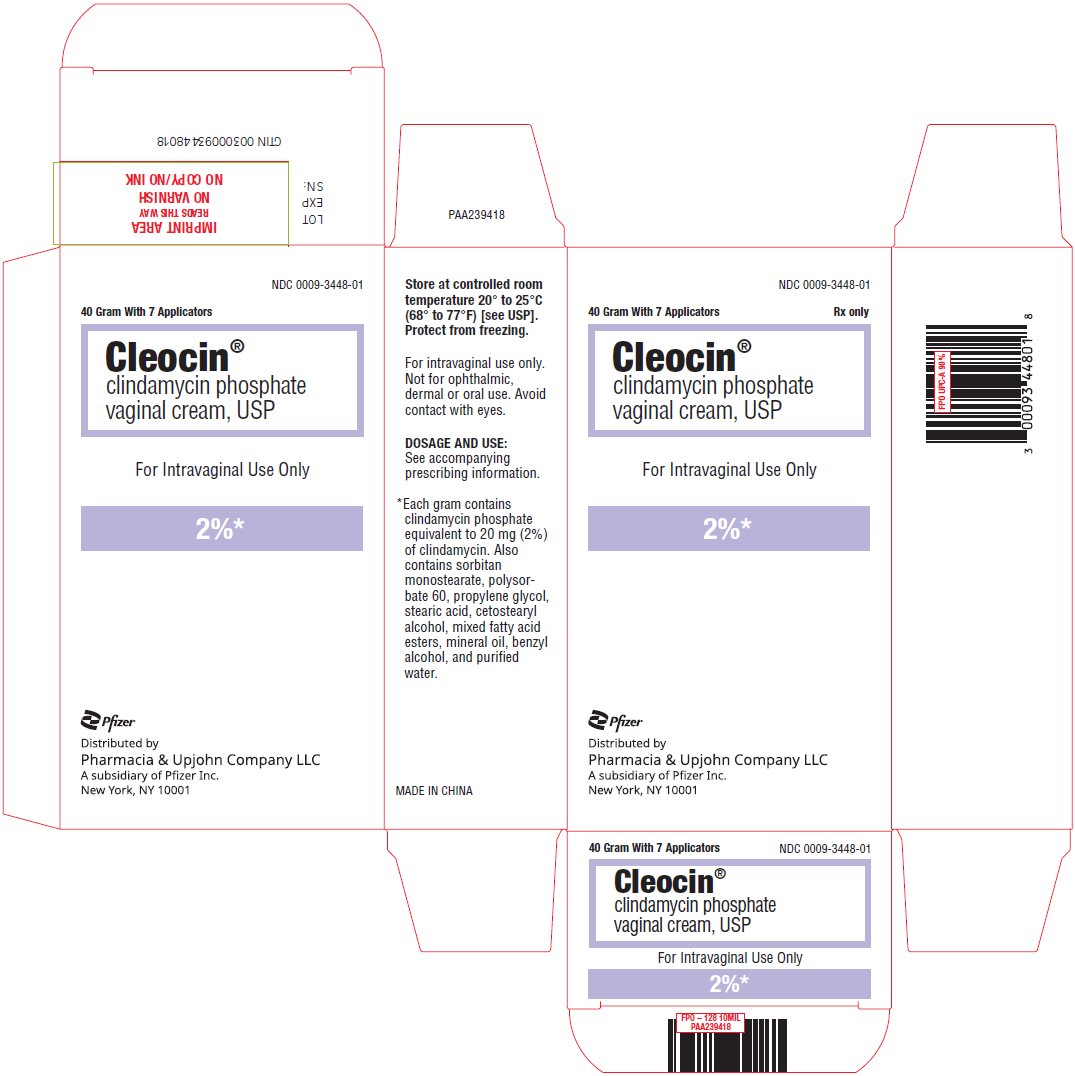 DRUG LABEL: Cleocin
NDC: 0009-3448 | Form: CREAM
Manufacturer: Pharmacia & Upjohn Company LLC
Category: prescription | Type: HUMAN PRESCRIPTION DRUG LABEL
Date: 20251119

ACTIVE INGREDIENTS: CLINDAMYCIN PHOSPHATE 20 mg/1 g
INACTIVE INGREDIENTS: BENZYL ALCOHOL; CETOSTEARYL ALCOHOL; MINERAL OIL; POLYSORBATE 60; PROPYLENE GLYCOL; WATER; SORBITAN MONOSTEARATE; STEARIC ACID

Cleocin®
clindamycin phosphate vaginal cream, USP

DESCRIPTION

Clindamycin phosphate is a water soluble ester of the semi-synthetic antibiotic produced by a 7(S)-chloro-substitution of the 7(R)-hydroxyl group of the parent antibiotic lincomycin. The chemical name for clindamycin phosphate is methyl 7-chloro-6,7,8-trideoxy-6-(1-methyl-trans-4-propyl-L-2-pyrrolidinecarboxamido)-1-thio-L-threo-α–D-galacto-octopyranoside 2-(dihydrogen phosphate). It has a molecular weight of 504.96, and the molecular formula is C18H34ClN2O8PS. The structural formula is represented below:

CLEOCIN Vaginal Cream 2%, is a semi-solid, white cream, which contains 2% clindamycin phosphate, USP, at a concentration equivalent to 20 mg clindamycin per gram. The pH of the cream is between 3.0 and 6.0. The cream also contains benzyl alcohol, cetostearyl alcohol, mixed fatty acid esters, mineral oil, polysorbate 60, propylene glycol, purified water, sorbitan monostearate, and stearic acid.

Each applicatorful of 5 grams of vaginal cream contains approximately 100 mg of clindamycin phosphate.

CLINICAL PHARMACOLOGY

Mechanism of Action

Clindamycin is an antibacterial drug (See MICROBIOLOGY).

Pharmacokinetics

Following a once a day intravaginal dose of 100 mg of clindamycin phosphate vaginal cream 2%, administered to 6 healthy female volunteers for 7 days, approximately 5% (range 0.6% to 11%) of the administered dose was absorbed systemically. The peak serum clindamycin concentration observed on the first day averaged 18 ng/mL (range 4 to 47 ng/mL) and on day 7 it averaged 25 ng/mL (range 6 to 61 ng/mL). These peak concentrations were attained approximately 10 hours post-dosing (range 4–24 hours).

Following a once a day intravaginal dose of 100 mg of clindamycin phosphate vaginal cream 2%, administered for 7 consecutive days to 5 women with bacterial vaginosis, absorption was slower and less variable than that observed in healthy females. Approximately 5% (range 2% to 8%) of the dose was absorbed systemically. The peak serum clindamycin concentration observed on the first day averaged 13 ng/mL (range 6 to 34 ng/mL) and on day 7 it averaged 16 ng/mL (range 7 to 26 ng/mL). These peak concentrations were attained approximately 14 hours post-dosing (range 4–24 hours).

There was little or no systemic accumulation of clindamycin after repeated vaginal dosing of clindamycin phosphate vaginal cream 2%. The systemic half-life was 1.5 to 2.6 hours.

MICROBIOLOGY

Mechanism of Action

Clindamycin inhibits bacterial protein synthesis by binding to the 23S RNA of the 50S subunit of the ribosome. Clindamycin is predominantly bacteriostatic. Although clindamycin phosphate is inactive in vitro, rapid in vivo hydrolysis converts it to active clindamycin.

Resistance

Resistance to clindamycin is most often caused by modification of the target site on the ribosome, usually by chemical modification of RNA bases by point mutations in RNA or occasionally in proteins. Cross resistance has been demonstrated between lincosamides, macrolides and streptogramins B in some organisms. Cross resistance has been demonstrated between clindamycin and lincomycin.

Antibacterial Activity

Culture and sensitivity testing of bacteria are not routinely performed to establish the diagnosis of bacterial vaginosis (see INDICATIONS AND USAGE); standard methodology for the susceptibility testing of the potential bacterial pathogens, Gardnerella vaginalis, Mobiluncus spp., or Mycoplasma hominis, has not been defined.

The following in vitro data are available but their clinical significance is unknown. Clindamycin is active in vitro against most isolates of the following organisms reported to be associated with bacterial vaginosis:

- Bacteroides spp.
- Gardnerella vaginalis
- Mobiluncus spp.
- Mycoplasma hominis
- Peptostreptococcus spp.

INDICATIONS AND USAGE

CLEOCIN Vaginal Cream 2%, is indicated in the treatment of bacterial vaginosis (formerly referred to as Haemophilus vaginitis, Gardnerella vaginitis, nonspecific vaginitis, Corynebacterium vaginitis, or anaerobic vaginosis). CLEOCIN Vaginal Cream 2%, can be used to treat non-pregnant women and pregnant women during the second and third trimester. (See CLINICAL STUDIES.)

NOTE: For purposes of this indication, a clinical diagnosis of bacterial vaginosis is usually defined by the presence of a homogeneous vaginal discharge that (a) has a pH of greater than 4.5, (b) emits a "fishy" amine odor when mixed with a 10% KOH solution, and (c) contains clue cells on microscopic examination. Gram's stain results consistent with a diagnosis of bacterial vaginosis include (a) markedly reduced or absent Lactobacillus morphology, (b) predominance of Gardnerella morphotype, and (c) absent or few white blood cells.

Other pathogens commonly associated with vulvovaginitis, eg, Trichomonas vaginalis, Chlamydia trachomatis, N. gonorrhoeae, Candida albicans, and Herpes simplex virus should be ruled out.

CONTRAINDICATIONS

CLEOCIN Vaginal Cream 2%, is contraindicated in individuals with a history of hypersensitivity to clindamycin, lincomycin, or any of the components of this vaginal cream. CLEOCIN Vaginal Cream 2%, is also contraindicated in individuals with a history of regional enteritis, ulcerative colitis, or a history of "antibiotic-associated" colitis.

WARNINGS

Pseudomembranous colitis has been reported with nearly all antibacterial agents, including clindamycin, and may range in severity from mild to life-threatening. Orally and parenterally administered clindamycin has been associated with severe colitis which may end fatally. Diarrhea, bloody diarrhea, and colitis (including pseudomembranous colitis) have been reported with the use of orally and parenterally administered clindamycin, as well as with topical (dermal and vaginal) formulations of clindamycin. Therefore, it is important to consider this diagnosis in patients who present with diarrhea subsequent to the administration of clindamycin, even when administered by the vaginal route, because approximately 5% of the clindamycin dose is systemically absorbed from the vagina.

Treatment with antibacterial agents alters the normal flora of the colon and may permit overgrowth of clostridia.Studies indicate that a toxin produced by Clostridioides difficile is a primary cause of "antibiotic-associated" colitis.

After the diagnosis of pseudomembranous colitis has been established, therapeutic measures should be initiated. Mild cases of pseudomembranous colitis usually respond to discontinuation of the drug alone. In moderate to severe cases, consideration should be given to management with fluids and electrolytes, protein supplementation, and treatment with an antibacterial drug clinically effective against Clostridioides difficile colitis.

Onset of pseudomembranous colitis symptoms may occur during or after antimicrobial treatment.

PRECAUTIONS

General

CLEOCIN Vaginal Cream 2%, contains ingredients that will cause burning and irritation of the eye. In the event of accidental contact with the eye, rinse the eye with copious amounts of cool tap water.

The use of CLEOCIN Vaginal Cream 2% may result in the overgrowth of nonsusceptible organisms in the vagina. In clinical studies involving 600 non-pregnant women who received treatment for 3 days, Candida albicans was detected, either symptomatically or by culture, in 8.8% of patients. In 9% of the patients, vaginitis was recorded. In clinical studies involving 1325 non-pregnant women who received treatment for 7 days, Candida albicans was detected, either symptomatically or by culture, in 10.5% of patients. Vaginitis was recorded in 10.7% of the patients. In 180 pregnant women who received treatment for 7 days, Candida albicans was detected, either symptomatically or by culture, in 13.3% of patients. In 7.2% of the patients, vaginitis was recorded. Candida albicans, as reported here, includes the terms: vaginal moniliasis and moniliasis (body as a whole). Vaginitis includes the terms: vulvovaginal disorder, vulvovaginitis, vaginal discharge, trichomonal vaginitis, and vaginitis.

Information for the Patient

The patient should be instructed not to engage in vaginal intercourse, or use other vaginal products (such as tampons or douches) during treatment with this product.

The patient should also be advised that this cream contains mineral oil that may weaken latex or rubber products such as condoms or vaginal contraceptive diaphragms. Therefore, use of such products within 72 hours following treatment with CLEOCIN Vaginal Cream 2%, is not recommended.

Drug Interactions

Systemic clindamycin has been shown to have neuromuscular blocking properties that may enhance the action of other neuromuscular blocking agents. Therefore, it should be used with caution in patients receiving such agents.

Carcinogenesis, Mutagenesis, Impairment of Fertility

Long term studies in animals have not been performed with clindamycin to evaluate carcinogenic potential.

Genotoxicity tests performed included a rat micronucleus test and an Ames test. Both tests were negative. Fertility studies in rats treated orally with up to 300 mg/kg/day (31 times the human exposure based on mg/m^2) revealed no effects on fertility or mating ability.

Pregnancy

Teratogenic effects

In clinical trials with pregnant women, the systemic administration of clindamycin during the second and third trimesters, has not been associated with an increased frequency of congenital abnormalities.

Clindamycin vaginal cream should be used during the first trimester of pregnancy only if clearly needed and the benefits outweigh the risks. There are no adequate and well-controlled studies in pregnant women during the first trimester of pregnancy.

CLEOCIN Vaginal Cream 2% has been studied in pregnant women during the second trimester. In women treated for seven days, abnormal labor was reported in 1.1% of patients who received clindamycin vaginal cream 2% compared with 0.5% of patients who received placebo.

Reproduction studies have been performed in rats and mice using oral and parenteral doses of clindamycin up to 600 mg/kg/day (62 and 25 times, respectively, the maximum human exposure based on body surface area) and have revealed no evidence of harm to the fetus due to clindamycin. Cleft palates were observed in fetuses from one mouse strain treated intraperitoneally with clindamycin at 200 mg/kg/day (about 10 times the recommended dose based on body surface area conversions). Since this effect was not observed in other mouse strains or in other species, the effect may be strain specific.

Nursing Mothers

Limited published data based on breast milk sampling reports that clindamycin appears in human breast milk in the range of less than 0.5 to 3.8 mcg/mL at dosages of 150 mg orally to 600 mg intravenously. It is not known if clindamycin is excreted in human breast milk following the use of vaginally administered clindamycin phosphate.

Clindamycin has the potential to cause adverse effects on the breast-fed infant's gastrointestinal flora. If clindamycin is required by a nursing mother, it is not a reason to discontinue breastfeeding, but an alternate drug may be preferred. Monitor the breast-fed infant for possible adverse effects on the gastrointestinal flora, such as diarrhea, candidiasis (thrush, diaper rash) or rarely, blood in the stool indicating possible antibiotic-associated colitis.

The developmental and health benefits of breastfeeding should be considered along with the mother's clinical need for clindamycin and any potential adverse effects on the breast-fed child from clindamycin or from the underlying maternal condition.

Pediatric Use

Safety and effectiveness in pediatric patients have not been established.

Geriatric Use

Clinical studies for CLEOCIN Vaginal Cream 2% did not include sufficient numbers of subjects aged 65 and over to determine whether they respond differently from younger subjects. Other reported clinical experience has not identified differences in responses between the elderly and younger patients.

ADVERSE REACTIONS

Clinical trials

Non-pregnant Women

In clinical trials involving non-pregnant women, 1.8% of 600 patients who received treatment with CLEOCIN Vaginal Cream 2% for 3 days and 2.7% of 1325 patients who received treatment for 7 days discontinued therapy due to drug-related adverse events. Medical events judged to be related, probably related, possibly related, or of unknown relationship to vaginally administered clindamycin phosphate vaginal cream 2%, were reported for 20.7% of the patients receiving treatment for 3 days and 21.3% of the patients receiving treatment for 7 days. Events occurring in ≥1% of patients receiving clindamycin phosphate vaginal cream 2% are shown in Table 1.

TABLE 1 – Events Occurring in ≥1% of Non-pregnant Patients Receiving Clindamycin Phosphate Vaginal Cream 2%
Event | CLEOCIN Vaginal Cream
Event | 3 Day n=600 | 7 Day n=1325
Urogenital
Vaginal moniliasis | 7.7 | 10.4
Vulvovaginitis | 6.0 | 4.4
Vulvovaginal disorder | 3.2 | 5.3
Trichomonal vaginitis | 0 | 1.3
Body as a Whole
Moniliasis (body) | 1.3 | 0.2

Other events occurring in <1% of the clindamycin vaginal cream 2% groups include:

Urogenital system: vaginal discharge, metrorrhagia, urinary tract infection, endometriosis, menstrual disorder, vaginitis/vaginal infection, and vaginal pain.

Body as a whole: localized abdominal pain, generalized abdominal pain, abdominal cramps, halitosis, headache, bacterial infection, inflammatory swelling, allergic reaction, and fungal infection.

Digestive system: nausea, vomiting, constipation, dyspepsia, flatulence, diarrhea, and gastrointestinal disorder.

Endocrine system: hyperthyroidism.

Central nervous system: dizziness and vertigo.

Respiratory system: epistaxis.

Skin: pruritus (non-application site), moniliasis, rash, maculopapular rash, erythema, and urticaria.

Special senses: taste perversion.

Pregnant Women

In a clinical trial involving pregnant women during the second trimester, 1.7% of 180 patients who received treatment for 7 days discontinued therapy due to drug-related adverse events. Medical events judged to be related, probably related, possibly related, or of unknown relationship to vaginally administered clindamycin phosphate vaginal cream 2%, were reported for 22.8% of pregnant patients. Events occurring in ≥1% of patients receiving either clindamycin phosphate vaginal cream 2% or placebo are shown in Table 2.

TABLE 2 - Events Occurring in ≥1% of Pregnant Patients Receiving Clindamycin Phosphate Vaginal Cream 2% or Placebo
Event | CLEOCIN Vaginal Cream | Placebo
Event | 7 DAY n=180 | 7 DAY n=184
Urogenital
Vaginal moniliasis | 13.3 | 7.1
Vulvovaginal disorder | 6.7 | 7.1
Abnormal labor | 1.1 | 0.5
Body as a Whole
Fungal infection | 1.7 | 0
Skin
Pruritus, non-application site | 1.1 | 0

Other events occurring in <1% of the clindamycin vaginal cream 2% group include:

Urogenital system: dysuria, metrorrhagia, vaginal pain, and trichomonal vaginitis.

Body as a whole: upper respiratory infection.

Skin: pruritus (topical application site) and erythema.

Post-marketing Experience

Because these reactions are reported voluntarily from a population of uncertain size, it is not always possible to reliably estimate their frequency or establish a causal relationship to drug exposure.

In the post-marketing period, there have been case reports of pseudomembranous colitis with the use of clindamycin phosphate vaginal cream.

Other clindamycin formulations

Clindamycin vaginal cream affords minimal peak serum levels and systemic exposure (AUCs) of clindamycin compared to 100 mg oral clindamycin dosing. Although these lower levels of exposure are less likely to produce the common reactions seen with oral clindamycin, the possibility of these and other reactions cannot be excluded presently. Data from well-controlled trials directly comparing clindamycin administered orally to clindamycin administered vaginally are not available.

The following adverse reactions and altered laboratory tests have been reported with the oral or parenteral use of clindamycin:

Infections and Infestations: Clostridioides difficile colitis

Gastrointestinal: Abdominal pain, esophagitis, nausea, vomiting, diarrhea, and pseudomembranous colitis. (See WARNINGS.)

Hematopoietic: Transient neutropenia (leukopenia), eosinophilia, agranulocytosis, and thrombocytopenia have been reported. No direct etiologic relationship to concurrent clindamycin therapy could be made in any of these reports.

Hypersensitivity Reactions: Maculopapular rash and urticaria have been observed during drug therapy. Generalized mild to moderate morbilliform-like skin rashes are the most frequently reported of all adverse reactions. Cases of Acute Generalized Exanthematous Pustulosis (AGEP), erythema multiforme, some resembling Stevens-Johnson syndrome, have been associated with clindamycin. A few cases of anaphylactoid reactions have been reported. If a hypersensitivity reaction occurs, the drug should be discontinued.

Liver: Jaundice and abnormalities in liver function tests have been observed during clindamycin therapy.

Musculoskeletal: Cases of polyarthritis have been reported.

Renal: Acute kidney injury

Immune System: Drug reaction with eosinophilia and systemic symptoms (DRESS) cases have been reported.

OVERDOSAGE

Vaginally applied clindamycin phosphate vaginal cream 2% could be absorbed in sufficient amounts to produce systemic effects. (See WARNINGS.)

DOSAGE AND ADMINISTRATION

The recommended dose is one applicatorful of clindamycin phosphate vaginal cream 2%, (5 grams containing approximately 100 mg of clindamycin phosphate) intravaginally, preferably at bedtime, for 3 or 7 consecutive days in non-pregnant patients and for 7 consecutive days in pregnant patients. (See CLINICAL STUDIES.)

HOW SUPPLIED

CLEOCIN Vaginal Cream 2%, (clindamycin phosphate vaginal cream) is supplied as follows:

40 g tube (with 7 disposable applicators) NDC 0009-3448-01

Store at controlled room temperature 20° to 25° C (68° to 77° F) [see USP]. Protect from freezing.

CLINICAL STUDIES

In two clinical studies involving 674 evaluable non-pregnant women with bacterial vaginosis comparing CLEOCIN Vaginal Cream 2% for 3 or 7 days, the clinical cure rates, determined at 1 month posttherapy, ranged from 72% to 81% for the 3-day treatment and 84% to 86% for the 7-day treatment.

 | CLEOCIN 3 Day |  | CLEOCIN 7 Day
US Study | 94/131 | 72% | 110/128 | 86%
European Study | 161/199 | 81% | 181/216 | 84%

In a clinical study involving 249 evaluable pregnant patients in the second and third trimester treated for 7 days, the clinical cure rate, determined at 1 month posttherapy, was 60% (77/129) in the clindamycin arm and 9% (11/120) for the vehicle arm. The determination of clinical cure was based on the absence of a "fishy" amine odor when the vaginal discharge was mixed with a 10% KOH solution and the absence of clue cells on microscopic examination.

Rx only

This product's labeling may have been updated. For the most recent prescribing information, please visit www.pfizer.com.

LAB-0043-15.0
Revised 3/2025

DIRECTIONS FOR USE

Disposable plastic applicators are provided with this package. They are designed to allow proper vaginal administration of the cream.

Remove cap from cream tube. Screw a plastic applicator on the threaded end of the tube.

Rolling tube from the bottom, squeeze gently and force the medication into the applicator. The applicator is filled when the plunger reaches its predetermined stopping point.

Unscrew the applicator from the tube and replace the cap.

While lying on your back, firmly grasp the applicator barrel and insert into vagina as far as possible without causing discomfort.

Slowly push the plunger until it stops.

Carefully withdraw applicator from vagina, and discard applicator.

REMEMBER TO APPLY ONE APPLICATORFUL EACH NIGHT BEFORE BEDTIME, OR AS PRESCRIBED BY YOUR DOCTOR.

INSTRUCCIONES PARA LA PACIENTE

Este envase contiene aplicadores de plástico desechables. Los aplicadores están diseñados para la administración apropiada de la crema en la vagina.

Remueva la tapa del tubo de crema y enrosque el aplicador de plástico al tubo.

Exprima el tubo suavemente desde el extremo inferior y fuerce el medicamento al aplicador. El aplicador estará lleno cuando el émbolo llega a su máxima longitud.

Desenrosque el aplicador del tubo y vuelva a poner la tapa.

Acuéstese de espalda y agarrando firmemente el aplicador, introdúzcalo en la vagina tanto como sea posible sin causar molestias.

Empuje lentamente el émbolo hasta que se detenga.

Saque el aplicador cuidadosamente de la vagina y descártelo.

RECUERDE APLICARSE UN APLICADOR LLENO TODAS LAS NOCHES AL ACOSTARSE, O DE ACUERDO CON LAS INDICACIONES DE SU MEDICO.

LAB-1058-1.0

PRINCIPAL DISPLAY PANEL - 40 g Tube Label

NDC 0009-3448-01

40 Gram
Rx only

Cleocin®
clindamycin phosphate
vaginal cream, USP

For Intravaginal Use Only

2%*

PRINCIPAL DISPLAY PANEL - 40 g Tube Carton

NDC 0009-3448-01

40 Gram With 7 Applicators
Rx only

Cleocin®
clindamycin phosphate
vaginal cream, USP

For Intravaginal Use Only

2%*

Pfizer
Distributed by
Pharmacia & Upjohn Company LLC
A subsidiary of Pfizer Inc.
New York, NY 10001